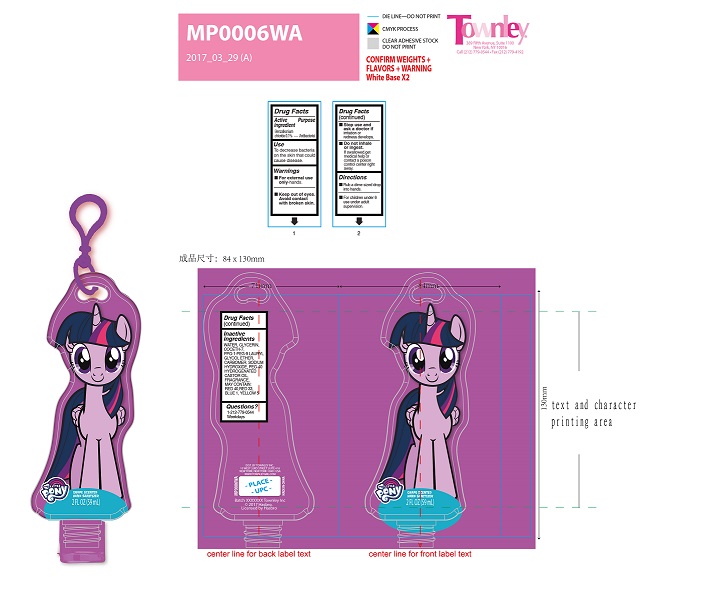 DRUG LABEL: Grape Scented Hand Sanitizer
NDC: 58737-218 | Form: GEL
Manufacturer: Townley, Inc.
Category: otc | Type: HUMAN OTC DRUG LABEL
Date: 20170810

ACTIVE INGREDIENTS: BENZALKONIUM CHLORIDE 1 g/59 g
INACTIVE INGREDIENTS: SODIUM HYDROXIDE; WATER; GLYCERIN; COCETH-7 CARBOXYLIC ACID; PPG-1 TRIDECETH-6; CARBOMER HOMOPOLYMER TYPE C (ALLYL PENTAERYTHRITOL CROSSLINKED); TROLAMINE; PEG-40 CASTOR OIL; PPG-1-PEG-9 LAURYL GLYCOL ETHER; METHOXY PEG-40; FD&C BLUE NO. 1; FD&C YELLOW NO. 5

Active Ingredient

Benzalkonium Chloride 0.1%

Purpose: Antibacterial

Use

To decrease bacteria on the skin that could cause disease.

Keep out of reach of children.

INDICATIONS AND USAGE

Disney Princess

Grape Scentend Hand Sanitizer

2 FL OZ (59mL)

Warnings

- for external use only-hands.
- keep out of eyes. avoid contact with broken skin.
- stop use and ask a Doctor if irritation or redness develops.
- do not inhale or ingest. if swallowed, get medical help or contact a poison control center right away.

Directions

- Rub a dime sized drop into hands.
- For children under 6 use under adult supervision.

Inactive Ingredients

water (aqua/eau), glycerin, coceth-7, PPG-1-PEG-9 lauryl glycol ether, carbomer, triethanolamine, PEG-40 hydrogenated castor oil, fragrance (parfum).

May Contain

Red 40 (CI 16035), Red 33 (CI 17200), Blue 1 (CI 42090), Yellow 5 (CI 19140).